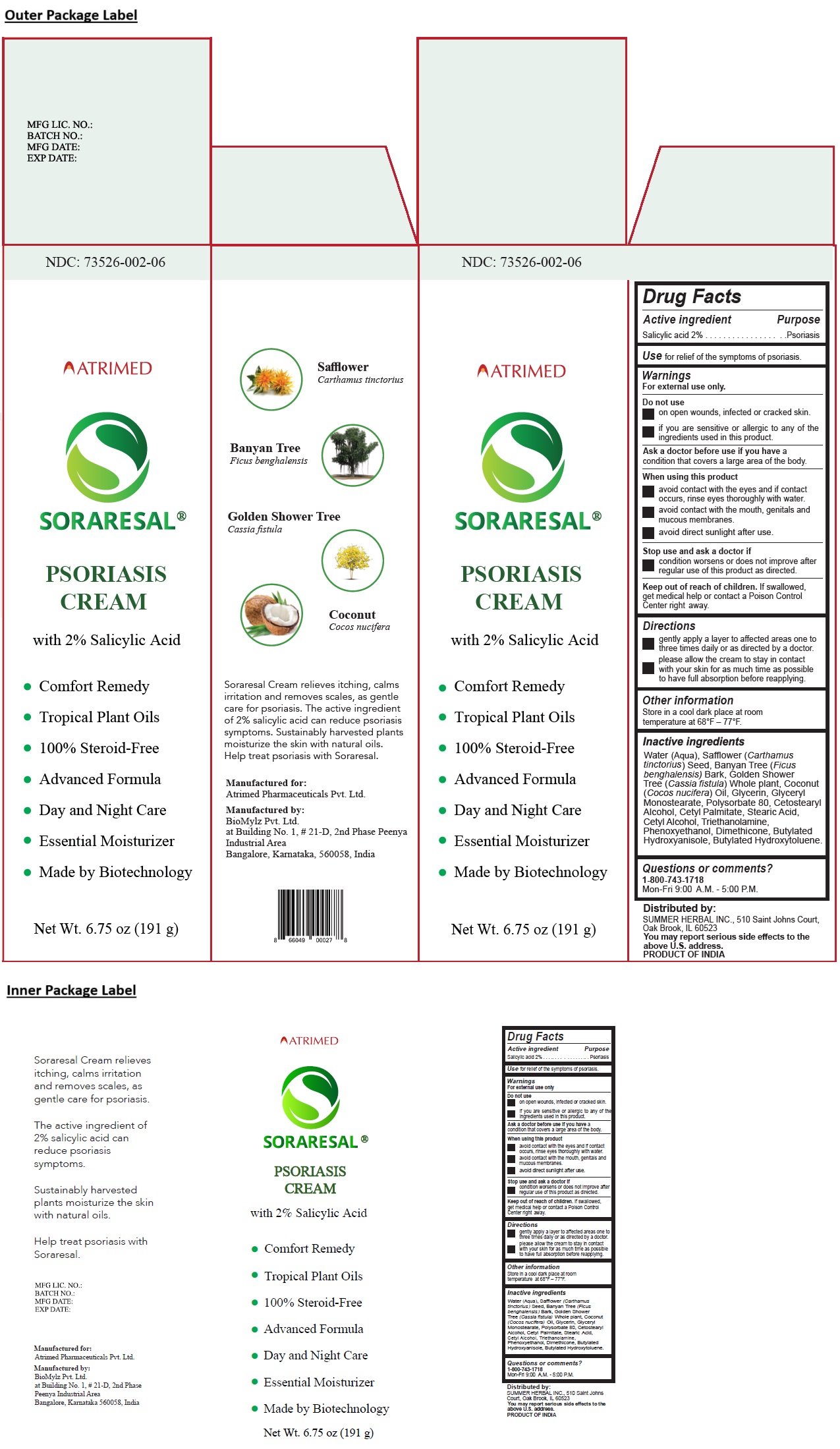 DRUG LABEL: SORARESAL
NDC: 73526-002 | Form: CREAM
Manufacturer: Summer Herbal Inc.
Category: otc | Type: HUMAN OTC DRUG LABEL
Date: 20240903

ACTIVE INGREDIENTS: SALICYLIC ACID 2 g/100 g
INACTIVE INGREDIENTS: WATER; SAFFLOWER OIL; FICUS BENGHALENSIS BARK; CASSIA FISTULA WHOLE; COCONUT OIL; GLYCERIN; GLYCERYL MONOSTEARATE; POLYSORBATE 80; CETOSTEARYL ALCOHOL; CETYL PALMITATE; STEARIC ACID; CETYL ALCOHOL; TROLAMINE; PHENOXYETHANOL; DIMETHICONE, UNSPECIFIED; BUTYLATED HYDROXYANISOLE; BUTYLATED HYDROXYTOLUENE

SORARESAL® PSORIASIS CREAM

Active ingredient

Salicylic acid 2%

Purpose

Psoriasis

Use

for relief of the symptoms of psoriasis.

Warnings

For external use only.

Do not use
• on open wounds, infected or cracked skin.
• if you are sensitive or allergic to any of the ingredients used in this product.

Ask a doctor before use if you have a condition that covers a large area of the body.

When using this product
• avoid contact with the eyes and if contact occurs, rinse eyes thoroughly with water.
• avoid contact with the mouth, genitals and mucous membranes.
• avoid direct sunlight after use.

Stop use and ask a doctor if
• condition worsens or does not improve after regular use of this product as directed.

Keep out of reach of children. If swallowed, get medical help or contact a Poison Control Center right away.

Directions

• gently apply a layer to affected areas one to three times daily or as directed by a doctor.
• please allow the cream to stay in contact with your skin for as much time as possible to have full absorption before reapplying.

Other information

Store in a cool dark place at room temperature at 68°F - 77°F.

Inactive ingredients

Water (Aqua), Safflower (Carthamus tinctorius) Seed, Banyan Tree (Ficus benghalensis) Bark, Golden Shower Tree (Cassia fistula) Whole plant, Coconut (Cocos nucifera) Oil, Glycerin, Glyceryl Monostearate, Polysorbate 80, Cetostearyl Alcohol, Cetyl Palmitate, Stearic Acid, Cetyl Alcohol, Triethanolamine, Phenoxyethanol, Dimethicone, Butylated Hydroxyanisole, Butylated Hydroxytoluene.

Questions or comments?

1-800-743-1718

Mon-Fri 9:00 A.M. - 5:00 P.M.

PSORIASIS CREAM

with 2% Salicylic Acid

• Comfort Remedy

• Tropical Plant Oils

• 100% Steroid-Free

• Advanced Formula

• Day and Night Care

• Essential Moisturizer

• Made by Biotechnology

Distributed by:
SUMMER HERBAL INC., 510 Saint Johns Court,
Oak Brook, IL 60523

You may report serious side effects to the above U.S. address.

PRODUCT OF INDIA

Soraresal Cream relieves itching, calms irritation and removes scales, as gentle care for psoriasis. The active ingredient of 2% salicylic acid can reduce psoriasis symptoms. Sustainably harvested plants moisturize the skin with natural oils. Help treat psoriasis with Soraresal.

Manufactured for:
Atrimed Pharmaceuticals Pvt. Ltd.

Manufactured by:
BioMylz Pvt. Ltd.
at Building No. 1, # 21-D, 2nd Phase
Peenya Industrial Area
Bangalore, Karnataka 560058, India